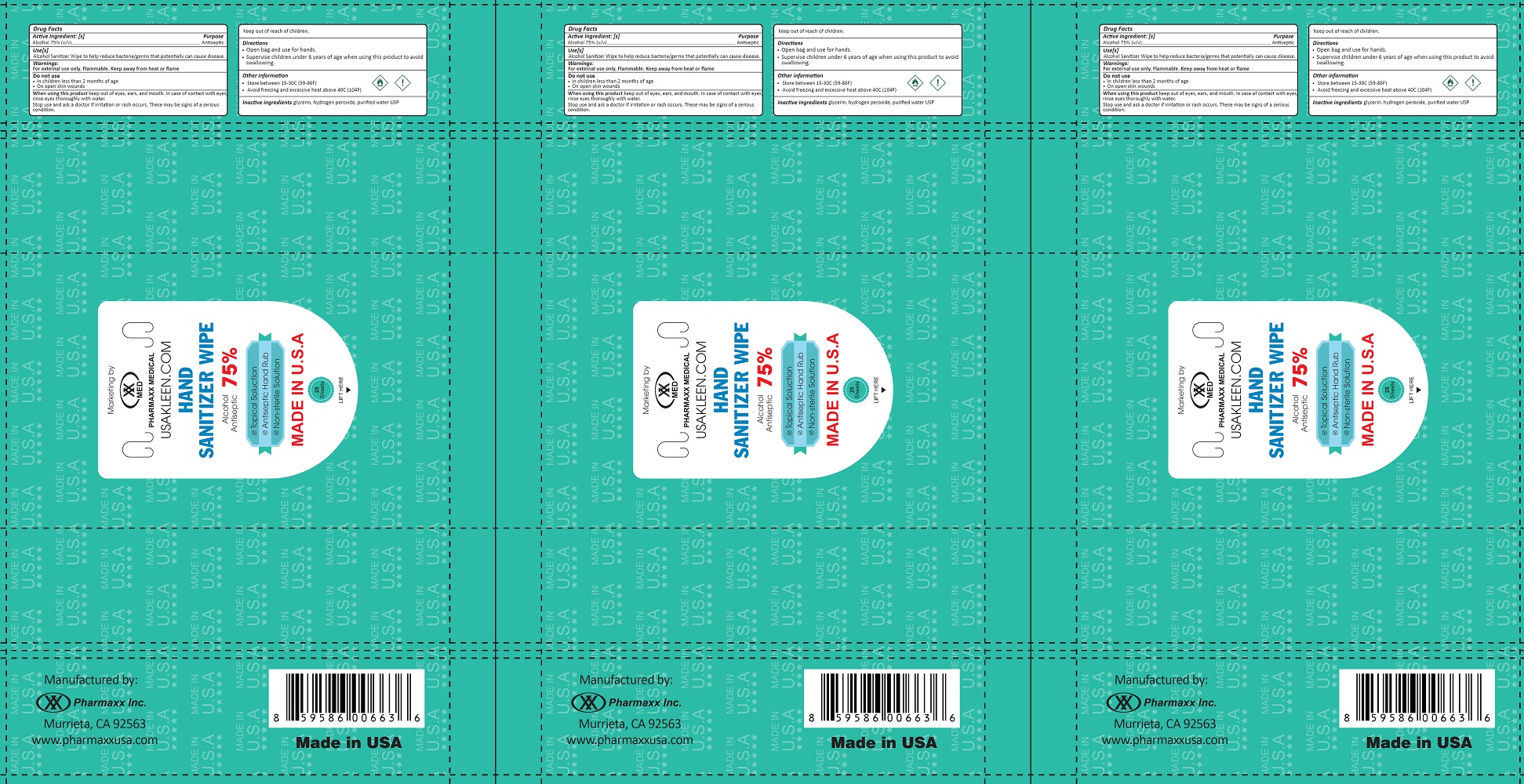 DRUG LABEL: Hand Sanitizer wipe 75%
NDC: 80066-663 | Form: CLOTH
Manufacturer: Pharmaxx, Inc.
Category: otc | Type: HUMAN OTC DRUG LABEL
Date: 20200831

ACTIVE INGREDIENTS: ALCOHOL 0.75 mL/1 mL
INACTIVE INGREDIENTS: GLYCERIN; HYDROGEN PEROXIDE; WATER

Hand Sanitizer wipe (75%)

Active ingredient: [s]

Alcohol 75% (v/v)

Purpose

Antiseptic

Use[s]

Alcohol Sanitizer Wipe to help reduce bacteria/germs that potentially can cause disease.

Warnings:

For external use only. Flammable. Keep away from heat or flame

Do not use

- In children less than 2 months of age
- on open skin wounds

When using this product

keep out of eyes, ears, and mouth. In case of contact with eyes, rinse eyes thoroughly with water.

Stop use and ask a doctor

if irritation or rash occurs. These may be signs of a serious condition.

Directions

- Open bag and use for hands.
- Supervise children under 6 years of age when using this product to avoid swallowing.

Other information

- Store between 15-30C (59-86F)
- Avoid freezing and excessive heat above 40C (104F)

Inactive ingredients

glycerin, hydrogen peroxide, purified water USP